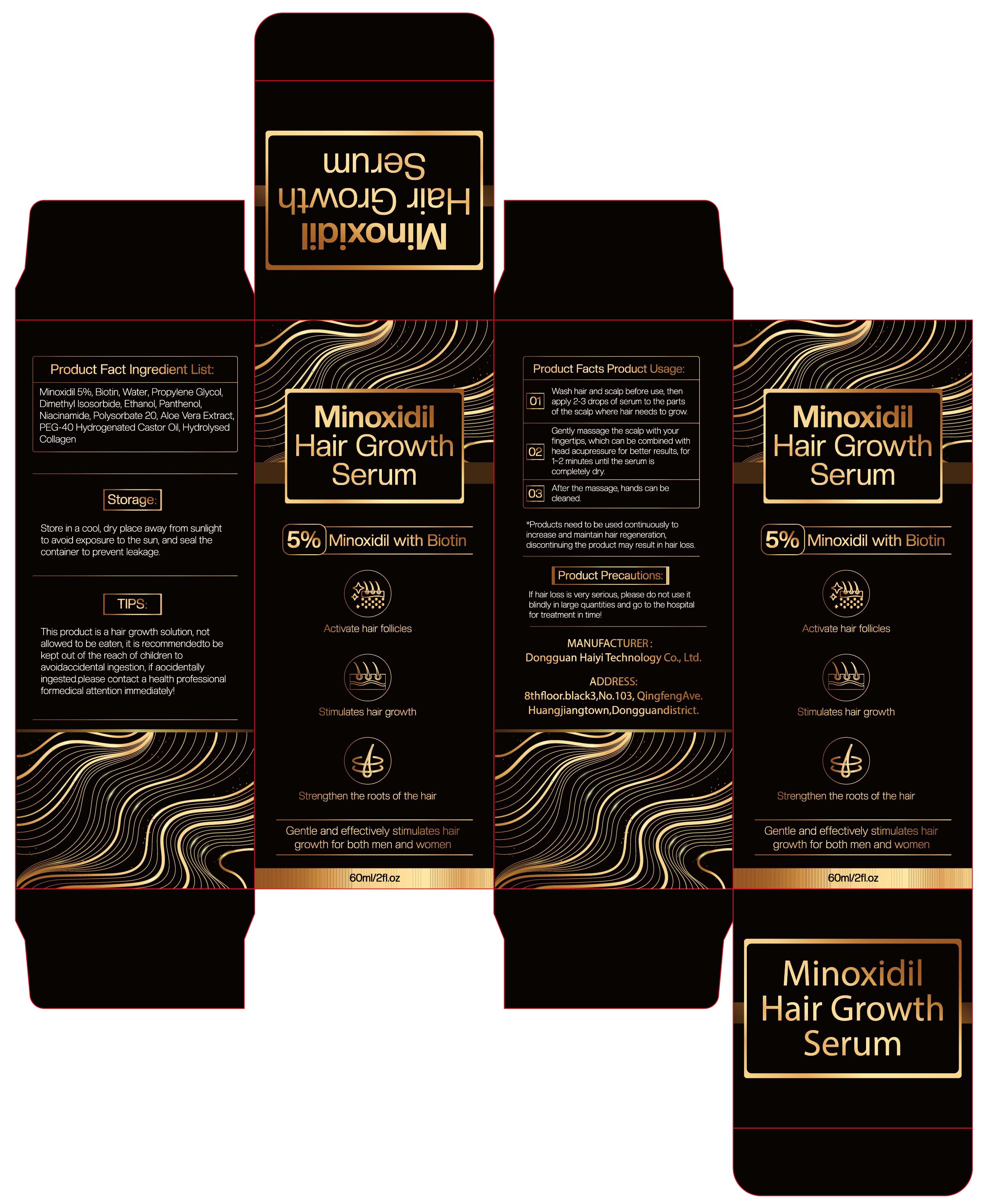 DRUG LABEL: Minoxidil Hair Growth Serum
NDC: 84732-089 | Form: LIQUID
Manufacturer: Dongguan Haiyi Technology Co.,Ltd.
Category: otc | Type: HUMAN OTC DRUG LABEL
Date: 20241108

ACTIVE INGREDIENTS: MINOXIDIL 5 mg/100 mL
INACTIVE INGREDIENTS: DIMETHYL ISOSORBIDE; WATER; ALCOHOL; PEG-40 HYDROGENATED CASTOR OIL; BIOTIN; NIACINAMIDE; POLYSORBATE 20; PANTHENOL; ALOE VERA LEAF; DIPROPYLENE GLYCOL

Active ingredient

Minoxidil 5%

Inactive ingredient

Biotin, Water, Propylene Glycol,Dimethyl lsosorbide, Ethanol, Panthenol,Niacinamide,Polysorbate 20, Aloe Vera Extract，PEG-40 Hydrogenated Castor Oil, Hydrolysed Collagen

Purpose section

1. Activate hair follicles
2. Stimulates hair growvth
3. Strengthen the roots of the hair
4. Gentle and effectively stimulates hairgrowth for both men and women

Warning

1. This product is a hair growth solution, notallowed to be eaten, it is recommended to bekept out of the reach of children toavoid accidental ingestion, if aocidentallyingested please contact a health professional formedical attention immediately
2. If hair loss is very serious, please do not use itblindly in large quantities and go to the hospitalfor treatment in time!

stop use

This product may cause allergic reactions in asmall number of people.
lf youexperience any discomfort,please stop using it immediately.

not use

Not suitable for use by children, pregnantor breast feeding people.

OUT OF CHILDREN

KEEP THE PRODUCT OUT OF REACH OF CHILDREN to

HOW TO USE

1. Wash hair and scalp before use, then apply 2-3 drops of serum to the parts of the scalp where hair needs to grow
2. Gently massage the scalp with your fingertips, which can be combined with head acupressure for better results, for 1~2 minutes until the serum is completety dry.
3. After the massage, hands can be cleaned.

Dosage

*Products need to be used continuously toincrease and maintain hair regeneration,<discontinuing the product may result in hair loss